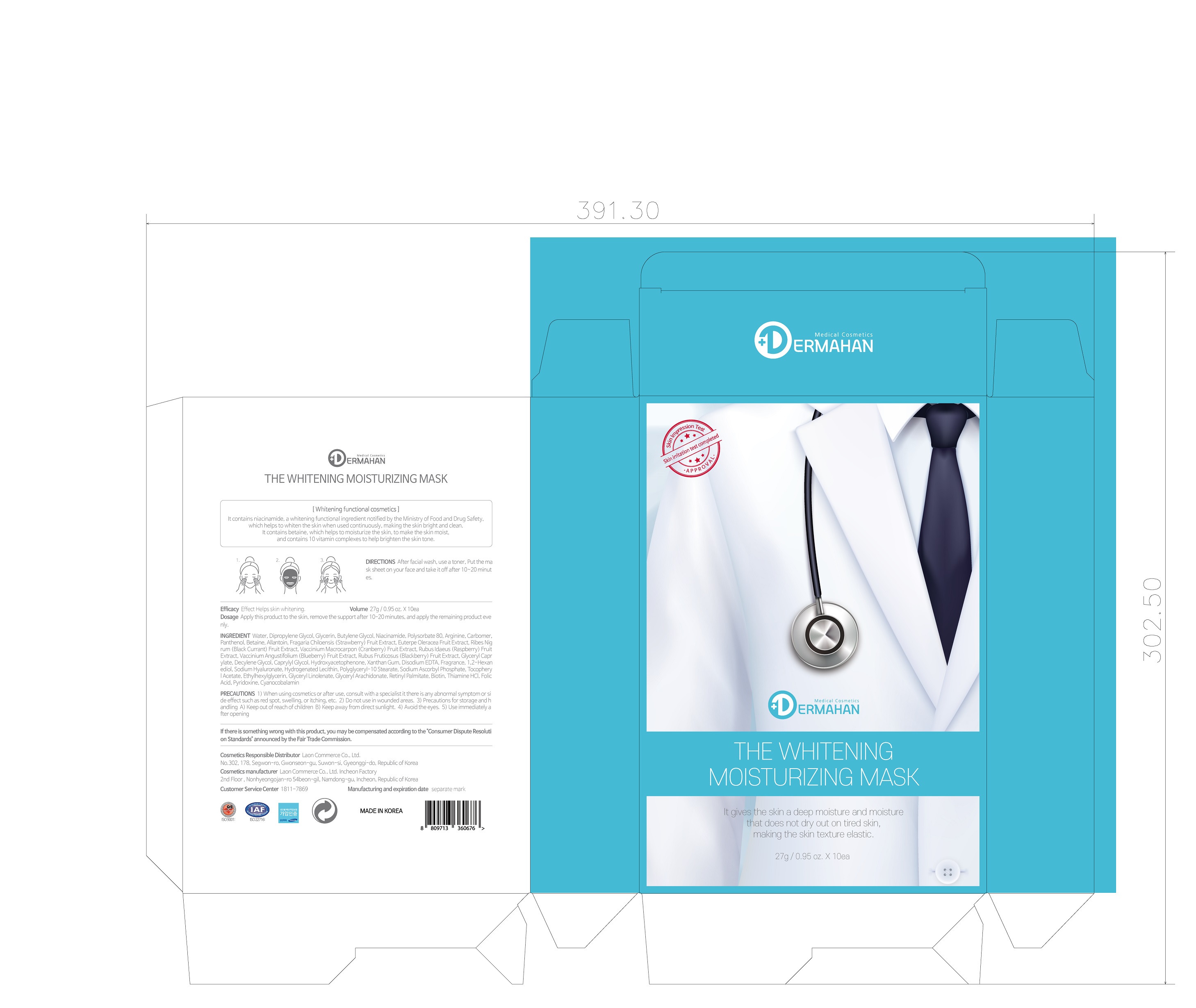 DRUG LABEL: DERMAHAN THE WHITENING MOISTURIZING MASK
NDC: 82083-0003 | Form: LIQUID
Manufacturer: LAON COMMERCE co ltd
Category: otc | Type: HUMAN OTC DRUG LABEL
Date: 20211024

ACTIVE INGREDIENTS: NIACINAMIDE 2 g/100 g
INACTIVE INGREDIENTS: WATER

ACTIVE INGREDIENT

niacinamide,

INACTIVE INGREDIENT

Water
Dipropylene Glycol
Glycerin
Butylene Glycol
Polysorbate 80
Arginine
Carbomer
Panthenol
Betaine
Allantoin
Fragaria Chiloensis (Strawberry) Fruit Extract
Euterpe Oleracea Fruit Extract
Ribes Nigrum (Black Currant) Fruit Extract
Vaccinium Macrocarpon (Cranberry) Fruit Extract
Rubus Idaeus (Raspberry) Fruit Extract
Vaccinium Angustifolium (Blueberry) Fruit Extract
Rubus Fruticosus (Blackberry) Fruit Extract
Glyceryl Caprylate
Decylene Glycol
Caprylyl Glycol
Hydroxyacetophenone
Xanthan Gum
Disodium EDTA
Fragrance
1,2-Hexanediol
Sodium Hyaluronate
Hydrogenated Lecithin
Polyglyceryl-10 Stearate
Sodium Ascorbyl Phosphate
Tocopheryl Acetate
Ethylhexylglycerin
Glyceryl Linolenate
Glyceryl Arachidonate
Retinyl Palmitate
Biotin
Thiamine HCl
Folic Acid
Pyridoxine
Cyanocobalamin

PURPOSE

whitening

WARNINGS

■ if following abnormal symptoms persist, discontinue use

Irritation around the eyes, ears, mucous membranes, including the mouth, under the skin irritation and rashes

■ Stop immediately and consult a doctor if you experience

1) Hypersensitivity symptoms such as erythema, itching and dermatitis.

2) Skin Irritation

3) Following Instructions when using medication

(1) For external use only (Do not use internally)

(2) Avoid getting into the eyes (if contact occurs, wash well with clean water)

Keep Out of Reach of Children.

INDICATIONS AND USAGE

After facial wash, use a toner, Put the ma

sk sheet on your face and take it off after 10~20 minutes.

DOSAGE AND ADMINISTRATION

for external use only